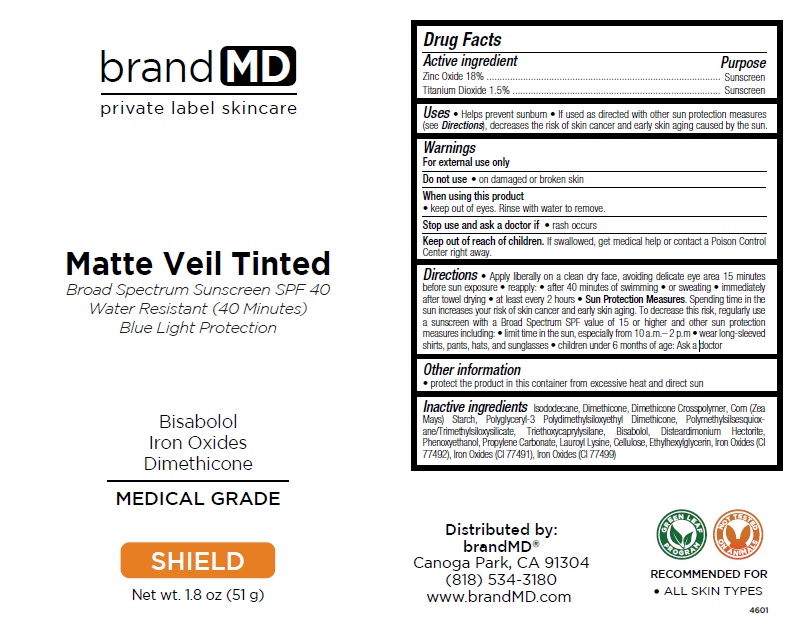 DRUG LABEL: Matte Veil Tinted Broad Spectrum Sunscreen SPF 40
NDC: 72957-010 | Form: CREAM
Manufacturer: Private Label Skin Care
Category: otc | Type: HUMAN OTC DRUG LABEL
Date: 20250226

ACTIVE INGREDIENTS: ZINC OXIDE 18 g/100 g; TITANIUM DIOXIDE 1.5 g/100 g
INACTIVE INGREDIENTS: ISODODECANE; DIMETHICONE, UNSPECIFIED; DIMETHICONE CROSSPOLYMER; STARCH, CORN; POLYGLYCERYL-3 POLYDIMETHYLSILOXYETHYL DIMETHICONE (4000 MPA.S); POLYMETHYLSILSESQUIOXANE/TRIMETHYLSILOXYSILICATE; TRIETHOXYCAPRYLYLSILANE; LEVOMENOL; DISTEARDIMONIUM HECTORITE; PHENOXYETHANOL; PROPYLENE CARBONATE; LAUROYL LYSINE; POWDERED CELLULOSE; ETHYLHEXYLGLYCERIN; FERRIC OXIDE YELLOW; FERRIC OXIDE RED; FERROSOFERRIC OXIDE

Matte Veil Tinted Broad Spectrum Sunscreen SPF 40

Active ingredient

Zinc Oxide 18%

Titanium Dioxide 1.5%

Purpose

Sunscreen

Uses

• Helps prevent sunburn • If used as directed with other sun protection measures (see Directions), decreases the risk of skin cancer and early skin aging caused by the sun.

Warnings

For external use only

Do not use • on damaged or broken skin

When using this product
• keep out of eyes. Rinse with water to remove.

Stop use and ask a doctor if • rash occurs

Keep out of reach of children. If swallowed, get medical help or contact a Poison Control Center right away.

Directions

• Apply liberally on a clean dry face, avoiding delicate eye area 15 minutes before sun exposure • reapply: • after 40 minutes of swimming • or sweating • immediately after towel drying • at least every 2 hours • Sun Protection Measures. Spending time in the sun increases your risk of skin cancer and early skin aging. To decrease this risk, regularly use a sunscreen with a Broad Spectrum SPF value of 15 or higher and other sun protection measures including: • limit time in the sun, especially from 10 a.m.– 2 p.m • wear long-sleeved shirts, pants, hats, and sunglasses • children under 6 months of age: Ask a doctor

Other information

• protect the product in this container from excessive heat and direct sun

Inactive ingredients

Isododecane, Dimethicone, Dimethicone Crosspolymer, Corn (Zea Mays) Starch, Polyglyceryl-3 Polydimethylsiloxyethyl Dimethicone, Polymethylsilsesquioxane/Trimethylsiloxysilicate, Triethoxycaprylysilane, Bisabolol, Disteardimonium Hectorite, Phenoxyethanol, Propylene Carbonate, Lauroyl Lysine, Cellulose, Ethylhexylglycerin, Iron Oxides (CI 77492), Iron Oxides (CI 77491), Iron Oxides (CI 77499)

brand MD

Water Resistant (40 Minutes)

Blue Light Protection

Bisabolol
Iron Oxides
Dimethicone

MEDICAL GRADE

SHIELD

GREEN LEAF PROGRAM

NOT TESTED ON ANIMALS

RECOMMENDED FOR
• ALL SKIN TYPES

Distributed by:
brandMD®
Canoga Park, CA 91304
(818) 534-3180
www.brandMD.com